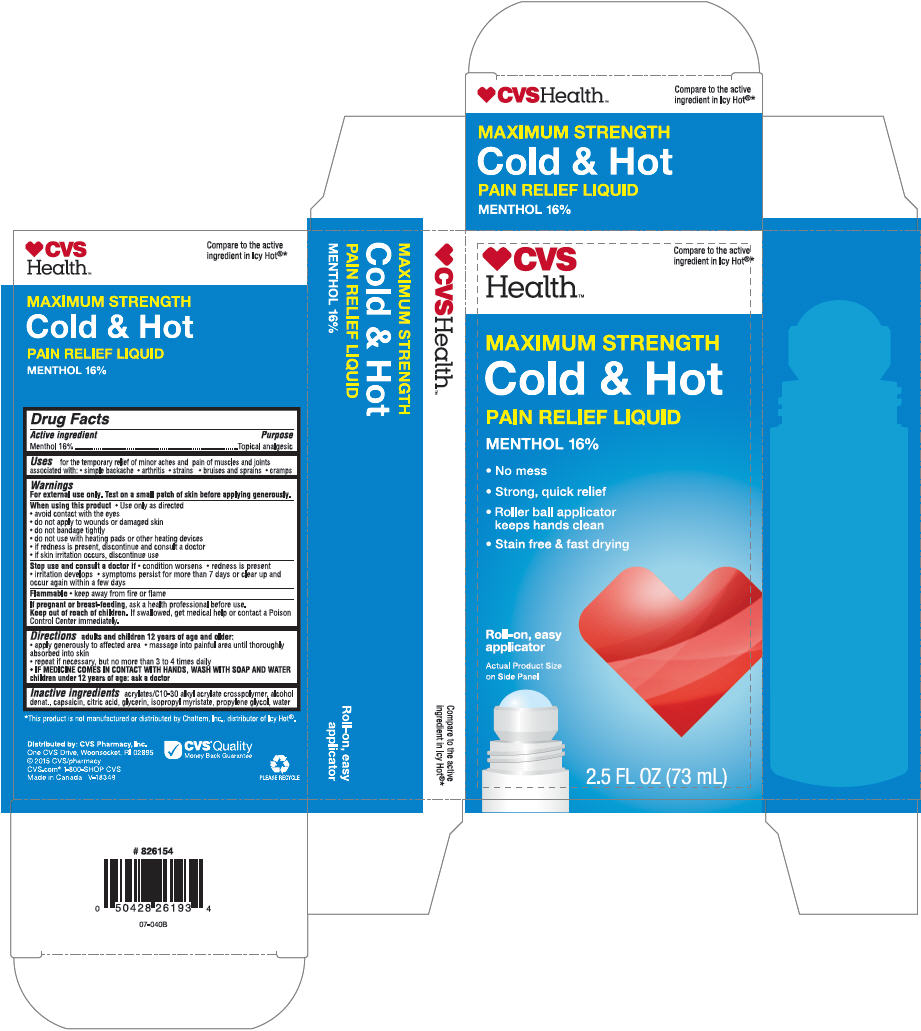 DRUG LABEL: CVS Maximum Strength Cold and Hot Pain Relief 
NDC: 69842-374 | Form: LIQUID
Manufacturer: CVS Health
Category: otc | Type: HUMAN OTC DRUG LABEL
Date: 20220125

ACTIVE INGREDIENTS: Menthol, Unspecified Form 160 mg/1 mL
INACTIVE INGREDIENTS: Carbomer Interpolymer Type A (Allyl Sucrose Crosslinked); Alcohol; Capsaicin; Citric Acid Monohydrate; Glycerin; Isopropyl Myristate; Propylene Glycol; Water

CVS Maximum Strength Cold & Hot Pain Relief Liquid
Topical Analgesic

Drug Facts

Active ingredients

Menthol 16.0%

Purpose

Topical Analgesic

Uses

for the temporary relief of minor aches and pain muscles and joints associated with:

♦ simple backache
♦ arthritis
♦ strains
♦ bruises and sprains
♦ cramps

Warnings

For external use only. Test on a small patch of skin before applying generously.

When using this product

♦ Use only as directed
♦ avoid contact with eyes
♦ do not apply to wounds or damages skin
♦ do not bandage tightly
♦ do not use with heating pads or other heating devices
♦ if redness is present, discontinue and consult a doctor
♦ if skin irritation occurs, discontinue use

Stop use and consult a doctor if

♦ condition worsens
♦ redness is present
♦ irritation develops
♦ symptoms persist for more than 7 days or clear up and occur again within a few days

Flammable

♦ keep away from fire or flame

PREGNANCY OR BREAST FEEDING

If pregnant or breast-feeding, as a health professional before use.

Keep out of reach of children. If swallowed, get medical help or contact a Poison Control Center right away.

Directions

adults and children 12 years of age and older:

♦ apply generously to affected area
♦ massage into painful area until thoroughly absorbed into skin
♦ repeat if necessary, but not more than 3 to 4 times daily
♦ IF MEDICINE COMES IN CONTACT WITH HANDS, WASH WITH SOAP AND WATER

children under 12 years of age: ask a doctor

Inactive ingredients

Acrylates/C10-30 Alkyl Acrylate Crosspolymer, Alcohol Denat., Capsaicin, Citric Acid, Glycerin, Isopropyl Myristate, Propylene Glycol, Water.

Distributed by: CVS Pharmacy, Inc.
One CVS Drive, Woonsocket, RI 02895

PRINCIPAL DISPLAY PANEL - 73 mL Cylinder Carton

♥CVS
Health™

Compare to the active
ingredient in Icy Hot®*

MAXIMUM STRENGTH
Cold & Hot
PAIN RELIEF LIQUID

MENTHOL 16%

- No mess
- Strong, quick relief
- Roller ball applicator
  keeps hands clean
- Stain free & fast drying

Roll-on, easy
applicator

Actual Product Size
on Side Panel

2.5 FL OZ (73 mL)